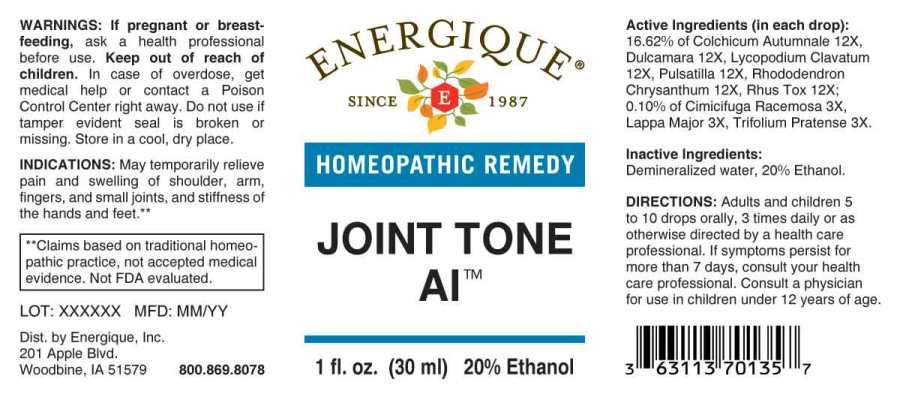 DRUG LABEL: Joint Tone AI
NDC: 44911-0587 | Form: LIQUID
Manufacturer: Energique, Inc.
Category: homeopathic | Type: HUMAN OTC DRUG LABEL
Date: 20231004

ACTIVE INGREDIENTS: BLACK COHOSH 3 [hp_X]/1 mL; ARCTIUM LAPPA ROOT 3 [hp_X]/1 mL; TRIFOLIUM PRATENSE FLOWER 3 [hp_X]/1 mL; COLCHICUM AUTUMNALE BULB 12 [hp_X]/1 mL; SOLANUM DULCAMARA TOP 12 [hp_X]/1 mL; LYCOPODIUM CLAVATUM SPORE 12 [hp_X]/1 mL; PULSATILLA PRATENSIS WHOLE 12 [hp_X]/1 mL; RHODODENDRON AUREUM LEAF 12 [hp_X]/1 mL; TOXICODENDRON PUBESCENS LEAF 12 [hp_X]/1 mL
INACTIVE INGREDIENTS: WATER; ALCOHOL

DRUG FACTS:

ACTIVE INGREDIENTS:

(in each drop): 16.62% of Colchicum Autumnale 12X, Dulcamara 12X, Lycopodium Clavatum 12X, Pulsatilla (Pratensis) 12X, Rhododendron Chrysanthum 12X, Rhus Tox 12X; 0.10% of Cimicifuga Racemosa 3X, Lappa Major 3X, Trifolium Pratense 3X.

INDICATIONS:

May temporarily relieve pain and swelling of shoulder, arm, fingers, and small joints, and stiffness of the hands and feet.**

**Claims based on traditional homeopathic practice, not accepted medical evidence. Not FDA evaluated.

WARNINGS:

If pregnant or breastfeeding, ask a health professional before use.

Keep out of reach of children. In case of overdose, get medical help or contact a Poison Control Center right away.

Do not use if tamper evident seal is broken or missing.

Store in a cool, dry place.

KEEP OUT OF REACH OF CHILDREN:

In case of overdose, get medical help or contact a Poison Control Center right away.

DIRECTIONS:

Adults and children 5 to 10 drops orally, 3 times daily or as otherwise directed by a health care professional. If symptoms persist for more than 7 days, consult your health care professional. Consult a physician for use in children under 12 years of age.

INDICATIONS:

May temporarily relieve pain and swelling of shoulder, arm, fingers, and small joints, and stiffness of the hands and feet.**

**Claims based on traditional homeopathic practice, not accepted medical evidence. Not FDA evaluated.

INACTIVE INGREDIENTS:

Demineralized water, 20% Ethanol.

QUESTIONS:

Dist. by Energique, Inc.
201 Apple Blvd.
Woodbine, IA 51579 800.869.8078

PACKAGE LABEL DISPLAY:

ENERGIQUE
SINCE 1987
HOMEOPATHIC REMEDY
JOINT TONE AI
1 fl. oz. (30 ml)